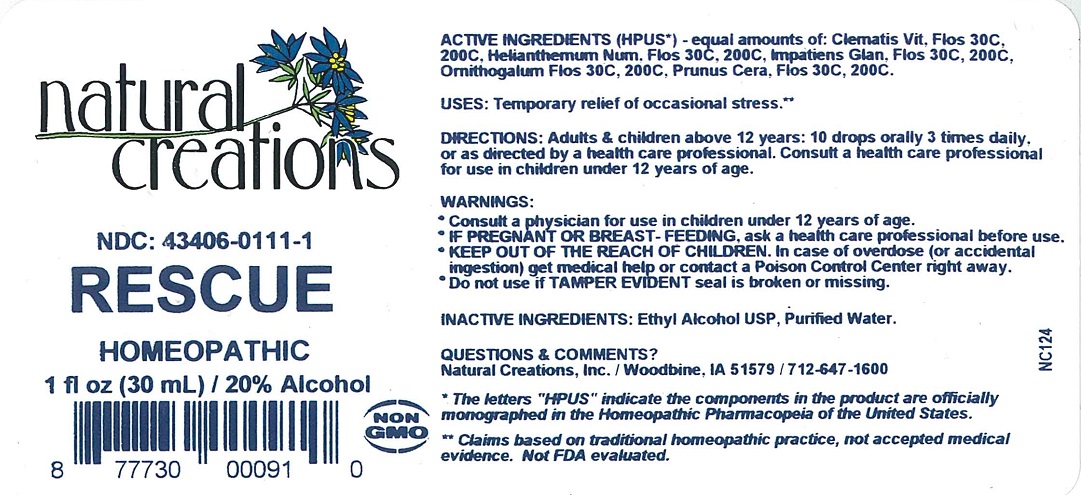 DRUG LABEL: RESCUE
NDC: 43406-0111 | Form: LIQUID
Manufacturer: Natural Creations, Inc
Category: homeopathic | Type: HUMAN OTC DRUG LABEL
Date: 20251216

ACTIVE INGREDIENTS: CLEMATIS VITALBA FLOWER 200 [hp_C]/1 mL; HELIANTHEMUM NUMMULARIUM FLOWER 200 [hp_C]/1 mL; IMPATIENS GLANDULIFERA FLOWER 200 [hp_C]/1 mL; ORNITHOGALUM UMBELLATUM FLOWERING TOP 200 [hp_C]/1 mL; PRUNUS CERASIFERA FLOWER 200 [hp_C]/1 mL
INACTIVE INGREDIENTS: ALCOHOL; WATER

RESCUE

ACTIVE INGREDIENT

ACTIVE INGREDIENTS (HPUS*) - equal amounts of: Clematis Vit, Flos 30C, 200C, Helianthemum Num, Flos 30C, 200C, Impatiens Glan, Flos 30C, 200C, Ornithogalum Flos 30C, 200C, Prunus Cera, Flos 30C, 200C.

INDICATIONS AND USAGE

USES: Temporary relief of occasional stress.**

PURPOSE

USES: Temporary relief of occasional stress.**

DOSAGE AND ADMINISTRATION

DIRECTIONS: Adults & children above 12 years: 10 drops orally 3 times daily, or as directed by a health care professional. Consult a health care professional in children under 12 years of age.

KEEP OUT OF REACH OF CHILDREN

KEEP OUT OF THE REACH OF CHILDREN. In case of overdose (or accidental ingestion) get medical help or contact a Poison Control Center right away.

WARNINGS:

- Consult a physician for use in children under 12 years of age.
- IF PREGNANT OR BREAST-FEEDING, ask a health care professional before use.
- KEEP OUT OF THE REACH OF CHILDREN. In case of overdose (or accidental ingestion) get medical help or contact a Poison Control Center right away.
- Do not use if TAMPER EVIDENT seal is broken or missing.

INACTIVE INGREDIENTS: Ethyl Alcohol USP, Purified Water.

QUESTIONS & COMMENTS?

Natural Creations, Inc. / Woodbine, IA 51579 / 712-647-1600

REFERENCES

*The letters "HPUS" indicate the components in the product are officialy monographed in the Homeopathic Pharmacopeia of the United States.

**Claims based on traditional homeopathic practice, not accepted medical evidence. Not FDA evaluated.

PACKAGE LABEL

NDC: 43406-0111-1

RESCUE

HOMEOPATHIC

1 fl oz (30 mL) / 20% Alcohol

877730000910